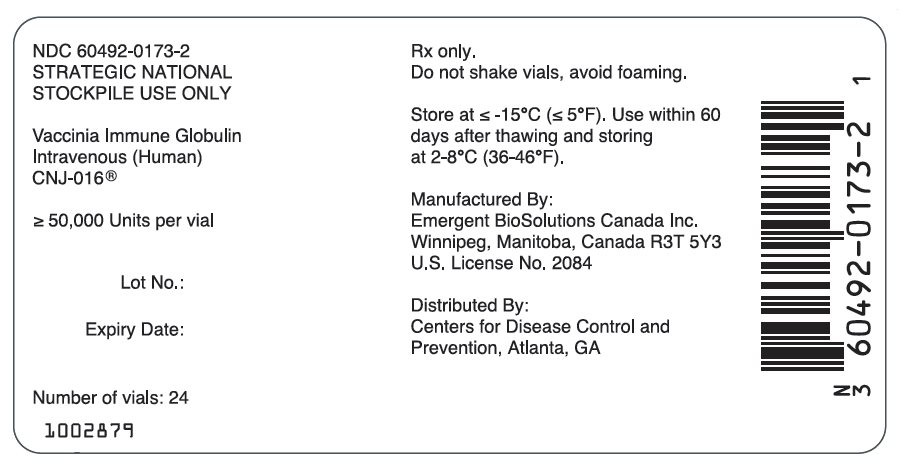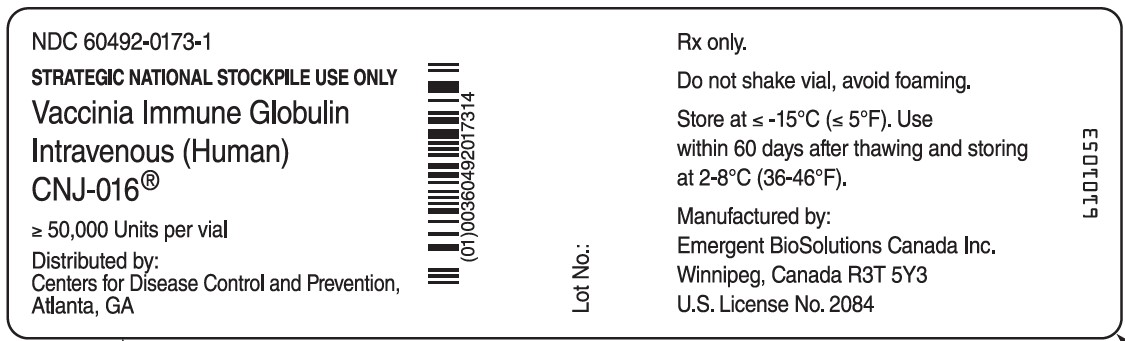 DRUG LABEL: CNJ-016
NDC: 60492-0173 | Form: INJECTION
Manufacturer: Emergent BioSolutions Canada Inc.
Category: prescription | Type: HUMAN PRESCRIPTION DRUG LABEL
Date: 20251216

ACTIVE INGREDIENTS: HUMAN VACCINIA VIRUS IMMUNE GLOBULIN 1 [iU]/1 mL
INACTIVE INGREDIENTS: MALTOSE MONOHYDRATE; POLYSORBATE 80

HIGHLIGHTS OF PRESCRIBING INFORMATION

These highlights do not include all the information needed to use CNJ-016® (vaccinia immune globulin intravenous, human), VIGIV safely and effectively. See full prescribing information for VIGIV.
VIGIV (vaccinia immune globulin, human), 5% solution for intravenous use.
Initial U.S. Approval: 2005

WARNING: INTERACTIONS WITH GLUCOSE MONITORING SYSTEMS

See full prescribing information for complete boxed warning.

Blood glucose measurement in patients receiving VIGIV (vaccinia immune globulin intravenous, human) must be done with a glucose-specific method (monitor and test strips) to avoid interference by maltose contained in VIGIV. Maltose in IGIV products may give falsely high blood glucose levels in certain types of blood glucose testing systems (for example those based on the GDH-PQQ or glucose-dye-oxidoreductase methods) resulting in inappropriate administration of insulin and life-threatening hypoglycemia. Cases of true hypoglycemia may go untreated if the hypoglycemic state is masked by falsely elevated glucose readings.

1 INDICATIONS AND USAGE

VIGIV is an Immune Globulin (Human), 5% Liquid, indicated for the treatment of complications due to vaccinia vaccination (1), including:

- Eczema vaccinatum
- Progressive vaccinia
- Severe generalized vaccinia
- Vaccinia infections in individuals who have skin conditions
- Aberrant infections induced by vaccinia virus (except in cases of isolated keratitis)

VIGIV is not indicated for postvaccinial encephalitis (1)

2 DOSAGE AND ADMINISTRATION

- For intravenous use only.
- VIGIV is administered at a dose of 6000 Units per kg, as soon as symptoms for complication(s) due to vaccinia vaccination appear (2.1).
- Higher doses (e.g. 9000 Units per kg or 24,000 Units per kg) may be considered in the event that the patient does not respond to the initial dose of 6000 Units per kg (2.1).
- For patients with risk factors for thrombosis, the maximum daily dose of VIGIV should not exceed 12,000 Units per kg (2.3).

3 DOSAGE FORMS AND STRENGTHS

Sterile solution available as 20 mL single-use vial containing a dose of ≥50,000 Units per vial (3).

4 CONTRAINDICATIONS

- Isolated vaccinia keratitis (4)
- History of anaphylactic or severe systemic reaction to human globulins (4)
- IgA deficiency with antibodies against IgA and a history of IgA hypersensitivity (4)

5 WARNINGS AND PRECAUTIONS

- Hypersensitivity to human immune globulin (acute anaphylaxis) (5.1)
- Acute renal dysfunction/failure (5.2)
- Thrombosis may occur with immune globulin products, including VIGIV. For patients at risk of thrombosis, administer VIGIV at the minimum dose and infusion rate practicable. Ensure adequate hydration in patients before administration. Monitor for signs and symptoms of thrombosis and assess blood viscosity in patients at risk for hyperviscosity (5.4)
- Hemolysis or hemolytic anemia (5.5)
- Aseptic meningitis syndrome (AMS) (5.6)
- Noncardiogenic pulmonary edema [Transfusion-Related Acute Lung Injury (TRALI)] (5.7)
- Transmission of infectious agents from human plasma (5.8)
- Monitor renal function and urine output in patients at risk of renal failure; check baseline blood viscosity in patients at risk of hyperviscosity; and conduct confirmatory tests if hemolysis or TRALI is suspected (5.9)

6 ADVERSE REACTIONS

The adverse drug reactions to VIGIV treatment in clinical trials (>10%) include headache, nausea, rigors and dizziness. (6)

To report SUSPECTED ADVERSE REACTIONS, contact Emergent BioSolutions Canada Inc. at 1-800-768-2304 or FDA at 1-800-FDA-1088 or www.fda.gov/medwatch.

7 DRUG INTERACTIONS

- Efficacy of live attenuated virus vaccines may be impaired by immune globulin administration; revaccination may be necessary (7.1)
- Antibodies in VIGIV may interfere with some serological tests (7.2)

FULL PRESCRIBING INFORMATION

WARNING: INTERACTIONS WITH GLUCOSE MONITORING SYSTEMS

Blood glucose measurement in patients receiving VIGIV must be done with a glucose-specific method (monitor and test strips) to avoid interference by maltose contained in VIGIV. Glucose dehydrogenase pyrroloquinolinequinone (GDH-PQQ) or glucose-dye-oxidoreductase method (monitor and test strips) must not be used for blood glucose testing in patients receiving VIGIV, since maltose in IGIV products has been shown to give falsely high blood glucose levels in these testing systems. This could result in the inappropriate administration of insulin, resulting in life-threatening hypoglycemia. Cases of true hypoglycemia may go untreated if the hypoglycemic state is masked by falsely elevated glucose readings.

Carefully review the product information of the blood glucose testing system, including that of the test strips, to determine if the system is appropriate for use with maltose-containing parenteral products [see 5.3 Blood Glucose Monitoring].

1 INDICATIONS AND USAGE

VIGIV (vaccinia immune globulin intravenous, human) is indicated for the treatment and/or modification of the following conditions:

- Eczema vaccinatum
- Progressive vaccinia
- Severe generalized vaccinia
- Vaccinia infections in individuals who have skin conditions such as burns, impetigo, varicella-zoster, or poison ivy; or in individuals who have eczematous skin lesions because of either the activity or extensiveness of such lesions
- Aberrant infections induced by vaccinia virus that include its accidental implantation in eyes (except in cases of isolated keratitis), mouth, or other areas where vaccinia infection would constitute a special hazard.

VIGIV is not considered to be effective in the treatment of postvaccinial encephalitis.

2 DOSAGE AND ADMINISTRATION

For intravenous use only.

2.1 Dosage for Treatment of Severe Complications of Vaccinia Vaccination

Administer VIGIV at a dose of 6000 Units per kg, as soon as symptoms appear and are judged to be due to severe vaccinia-related complication. Consider repeat dosing, depending on the severity of the symptoms and response to treatment; however, clinical data on repeat doses are lacking. Consider higher doses (e.g. 9000 Units per kg) if the patient does not respond to the initial 6000 Units per kg dose. Doses up to 24,000 Units per kg administered to healthy volunteers were well tolerated in clinical trials [see 14 CLINICAL STUDIES].

2.2 Preparation

- Bring VIGIV vials to room temperature prior to dosing.
  - If frozen, thaw vial by placing in a refrigerator at 2°C to 8°C (36°F to 46°F) until the contents are thawed for approximately 14 hours. Product can be thawed rapidly by placing at room temperature for one hour followed by a water bath at 37°C (98.6°F) until thawed.
  - Do not thaw this product in a microwave oven.
  - Do not refreeze the vial.
- DO NOT SHAKE VIAL. SHAKING VIAL MAY CAUSE FOAMING.
- Remove the entire contents of the vial to obtain the labeled dosage of VIGIV. If partial vials are required for the dosage calculation, withdraw the entire contents of the vial to ensure accurate calculation of the dosage requirement.
- VIGIV is compatible with 0.9% Sodium Chloride USP. No other drug interactions or compatibilities have been evaluated. If a pre-existing catheter must be used, flush the line with 0.9% Sodium Chloride USP before use. VIGIV may be administered either undiluted or diluted no more than 1:2 (v/v).
- VIGIV vial is for single use only. Do not reuse or save VIGIV for future use.
- VIGIV contains no preservatives. Discard partially used vials.

2.3 Administration

- Inspect the product prior to use and do not use if solution is cloudy, discolored or contains particulates.
- Administer VIGIV intravenously through a dedicated intravenous line with the rate of infusion of no greater than 2 mL/min.
- For patients weighing less than 50 kg, infuse the product at a rate no greater than 0.04 mL/kg/minute (133.3 Units per kg/minute).
- Adverse drug reactions may be related to the rate of infusion. Slower infusion rate may be needed for patients who develop a minor adverse reaction (e.g. flushing) or for patients with risk factors for thrombosis/thromboembolism.
- Closely monitor and carefully observe patients and their vital signs for any symptoms throughout the infusion period and immediately following an infusion.
- For patients with pre-existing renal insufficiency, or at increased risk of acute kidney injury, thrombosis, or volume overload, do not exceed the recommended infusion rate and follow the infusion schedule closely.
- For patients with risk factors for thrombosis, the maximum daily dose of VIGIV should not exceed 12,000 Units per kg [see 5.4 Thrombosis].

3 DOSAGE FORMS AND STRENGTHS

- Solution of gamma globulin (5% or 50 mg/mL)
- 20 mL single-dose vial containing antibodies to vaccinia virus at ≥50,000 Units per vial

4 CONTRAINDICATIONS

VIGIV is contraindicated in:

- Isolated vaccinia keratitis.
- Individuals with a history of anaphylaxis or prior severe systemic reaction associated with the parenteral administration of this or other human immune globulin preparations.
- IgA-deficient patients with antibodies against IgA and a history of IgA hypersensitivity, as it contains trace amounts of IgA (40 mcg/mL).

5 WARNINGS AND PRECAUTIONS

5.1 Hypersensitivity

Severe immediate hypersensitivity reactions to plasma-derived products may occur, for example, in patients with IgA deficiency or hypersensitivity to human globulin. Although acute systemic allergic reactions were not seen in clinical trials with VIGIV [see 6.1 Clinical Trials Experience], administer the product only in a setting where appropriate equipment and personnel trained in the management of acute anaphylaxis are available. In case of hypotension, allergic or anaphylactic reaction, discontinue the administration of VIGIV immediately and give supportive care as needed. In case of shock, observe the current medical standards for shock treatment.

5.2 Acute Renal Dysfunction/Failure

Renal dysfunction, acute renal failure, osmotic nephropathy, proximal tubular nephropathy, and death may occur upon use of immune globulin intravenous (Human) (IGIV) products. Use VIGIV with caution in patients with pre-existing renal insufficiency and in patients at risk of developing renal insufficiency (including, but not limited to those with diabetes mellitus, age greater than 65 years, volume depletion, paraproteinemia, sepsis, and patients receiving known nephrotoxic drugs), and administer VIGIV at the minimum rate of infusion practicable. In these cases, it is important to ensure that patients are not volume depleted before VIGIV infusion. Do not exceed the recommended infusion rate and follow the infusion schedule closely [see 2.3 Administration]. Periodic monitoring of renal function and urine output is particularly important in patients judged to be at increased risk of developing acute renal failure. Assess renal function, including measurement of blood urea nitrogen (BUN) and serum creatinine, before the initial infusion of VIGIV and at appropriate intervals thereafter. If renal function deteriorates, consider discontinuing VIGIV.

Most cases of renal insufficiency following administration of IGIV have occurred in patients receiving total doses containing 400 mg/kg of sucrose or greater. VIGIV does not contain sucrose. No prospective data are currently available in patients with risk factors for renal insufficiency to identify a maximum safe dose, concentration, and/or rate of infusion for VIGIV.

5.3 Blood Glucose Monitoring

Some types of blood glucose testing systems (for example those based on the glucose dehydrogenase pyrroloquinolinequinone (GDH-PQQ) or glucose-dye-oxidoreductase methods) could falsely interpret the maltose contained in VIGIV as glucose [see BOXED WARNING]. This could result in falsely elevated glucose readings and, consequently, in the inappropriate administration of insulin, resulting in life-threatening hypoglycemia. Also, cases of true hypoglycemia may go untreated if the hypoglycemic state is masked by falsely elevated glucose readings. Accordingly, when administering VIGIV or other parenteral maltose-containing products, measure blood glucose with a glucose-specific method.

Carefully review the product information of the blood glucose testing system, including that of the test strips, to determine if the system is appropriate for use with maltose-containing parenteral products. If any uncertainty exists, contact the manufacturer of the testing system to determine if the system is appropriate for use with maltose-containing parenteral products.

5.4 Thrombosis

Thrombotic events may occur in association with IGIV treatment. Patients at risk include those with a history of cardiovascular risk factors, advanced age, impaired cardiac output, hypercoagulable disorders, prolonged periods of immobilization, history of arterial or venous thrombosis, estrogen use, indwelling central vascular catheters, and/or known or suspected hyperviscosity. Weigh the potential risks and benefits of VIGIV against those of alternative therapies for all patients for whom VIGIV administration is being considered.

Because of the potentially increased risk of thrombosis, consider baseline assessment of blood viscosity in patients at risk for hyperviscosity, including those with cryoglobulins, fasting chylomicronemia/markedly high triacylglycerols (triglycerides), or monoclonal gammopathies.

In patients where the benefits of VIGIV administration out-weigh the potential risks of thrombotic and thromboembolic events, administer VIGIV at the minimum concentration available and at the minimum rate of infusion practicable. Ensure adequate hydration in patients before administration. Monitor for signs and symptoms of thrombosis and assess blood viscosity in patients at risk for hyperviscosity. While there are currently no prospective data in patients with thrombosis/thromboembolism to identify a maximum safe dose, concentration, and/or rate of infusion for VIGIV, the maximum daily dose of VIGIV should not exceed 12,000 Units per kg in patients with thrombotic risk factors.

5.5 Hemolysis

VIGIV may contain blood group antibodies which may act as hemolysins and induce in vivo coating of red blood cells with immune globulin, causing a positive direct antiglobulin reaction and hemolysis. Acute hemolysis, consistent with intravascular hemolysis, has been reported and hemolytic anemia can develop subsequent to IGIV therapy due to enhanced red blood cell sequestration.

The following risk factors may be associated with the development of hemolysis following Immune Globulin Intravenous (Human) (IGIV) products: high doses, given either as a single administration or divided over several days, and non-O blood group (1). Other individual patient factors, such as an underlying inflammatory state (as may be reflected by, for example, elevated C-reactive protein or erythrocyte sedimentation rate), have been hypothesized to increase the risk of hemolysis following administration of IGIV (2), but their role is uncertain. Closely monitor VIGIV recipients for clinical signs and symptoms of hemolysis, particularly patients with risk factors noted above. Consider appropriate laboratory testing in higher risk patients, including measurement of hemoglobin or hematocrit prior to infusion and within approximately 36 to 96 hours post infusion. If signs and/or symptoms of hemolysis or a significant drop in hemoglobin or hematocrit have been observed after VIGIV infusion, perform additional confirmatory laboratory testing. If transfusion is indicated for patients who develop hemolysis with clinically compromising anemia after receiving VIGIV, perform adequate cross-matching to avoid exacerbating on-going hemolysis.

5.6 Aseptic Meningitis Syndrome (AMS)

AMS may occur in association with IGIV administration. AMS usually begins within several hours to two days following IGIV treatment. Discontinuation of IGIV treatment has resulted in remission of AMS within several days without sequelae.

AMS is characterized by the following symptoms and signs: severe headache, nuchal rigidity, drowsiness, fever, photophobia, painful eye movements, and nausea and vomiting. Cerebrospinal fluid (CSF) studies are frequently positive with pleocytosis up to several thousand cells per cubic millimeter, predominately from the granulocytic series, and with elevated protein levels up to several hundred mg/dL, but negative culture results. Conduct a thorough neurological examination in patients exhibiting such symptoms and signs, including CSF studies, to rule out other causes of meningitis.

AMS may occur more frequently in association with high total doses (2 g/kg) of IGIV treatment. For VIGIV, at the recommended dosage of 6000 Units per kg, a patient may be exposed to up to 0.18 g/kg protein after VIGIV administration.

5.7 Transfusion-related Acute Lung Injury (TRALI)

Noncardiogenic pulmonary edema may occur in patients administered IGIV. TRALI is characterized by severe respiratory distress, pulmonary edema, hypoxemia, normal left ventricular function, and fever and typically occurs within one to six hours after transfusion. Patients with TRALI may be managed using oxygen therapy with adequate ventilatory support.

Monitor VIGIV recipients for pulmonary adverse reactions. If TRALI is suspected, perform appropriate tests for the presence of anti-neutrophil antibodies in both the product and patient serum.

5.8 Transmissible Infectious Agents

Because this product is made from human blood, it may carry a risk of transmitting infectious agents, e.g., viruses, the variant Creutzfeldt‐Jakob disease (vCJD) agent and, theoretically, the Creutzfeldt‐Jakob disease (CJD) agent.

All infections thought to have been possibly transmitted by this product should be reported by the physician or other health care provider to Emergent BioSolutions Canada Inc. at 1 800-768-2304.

5.9 Monitoring: Laboratory Tests

- Periodic monitoring of renal function and urine output is particularly important in patients judged to be at increased risk of developing acute renal failure. Assess renal function, including measurement of BUN and serum creatinine, before the initial infusion of VIGIV and at appropriate intervals thereafter.
- Because of the potentially increased risk of thrombosis, consider baseline assessment of blood viscosity in patients at risk for hyperviscosity, including those with cryoglobulins, fasting chylomicronemia/markedly high triacylglycerols (triglycerides), or monoclonal gammopathies.
- If signs and/or symptoms of hemolysis are present after an infusion of VIGIV, perform appropriate laboratory testing for confirmation.
- If TRALI is suspected, perform appropriate tests for the presence of anti-neutrophil antibodies in both the product and patient’s serum.

6 ADVERSE REACTIONS

The adverse drug reactions to VIGIV treatment in clinical trials (>10%) include headache, nausea, rigors and dizziness.

6.1 Clinical Trials Experience

Because clinical trials are conducted under widely varying conditions, adverse reaction rates observed in the clinical trials of a drug cannot be directly compared to rates in the clinical trials of another drug and may not reflect the rates observed in practice.

In a safety/pharmacokinetics study, 60 healthy male and female volunteers received a single intravenous dose of either 6000 Units per kg or 9000 Units per kg VIGIV. The population consisted of vaccinia vaccination-naïve subjects, ages 18 to 32, with both males and females enrolled in an approximate 50:50 ratio.

In a pharmacodynamic study, 32 healthy male and female volunteers were randomized to receive vaccinia vaccination (n=10), VIGIV (9000 Units per kg) 4 days prior to vaccinia vaccination (n=10), or VIGIV (9000 Units per kg) concurrent with vaccinia vaccination (n=12). The population consisted of vaccinia vaccination-naïve subjects, ages 18 to 32, with both male and female enrolled in a 75:25 ratio. The ethnic background of patients included those of Caucasian, African American, Asian and Hispanic descent, with the majority of them being Caucasian.

In an additional pharmacodynamic clinical study, 50 healthy male and female volunteers were randomized to receive VIGIV at 9000 Units per kg (n=20) or at 24,000 Units per kg (n=20) or placebo (n=10) 4 days prior to vaccinia vaccination (n=30) or placebo (n=20). The population consisted of vaccinia vaccination-naïve male and female subjects, ages 18 to 33, in a 60:40 ratio. The ethnic background of patients included those of Caucasian, African American, and Hispanic descent, with the majority of them being African American.

The most frequently reported adverse reactions related to VIGIV administration in all three clinical studies were headache, nausea, rigors, and dizziness. Table 1 describes the adverse reactions that were temporally related to VIGIV or placebo administration that occurred during or within three days of product infusion with a frequency of 5% or higher in any one treatment group.

Table 1 Adverse Drug Reactions that Occurred Temporally* During or Following VIGIV Administration (≥5%)
SYSTEM ORGAN CLASS | PREFERRED TERM | VIGIV (%) 6000 U/kgb N=31 | VIGIV (%) 9000 U/kgc N=39 | VIGIV (%) 9000 U/kgd N=20 | VIGIV (%) 24,000 U/kgd N=20 | PLACEBOa N=32 (%)
All Body System | All Preferred Terms | 19 (61.3) | 30 (76.9) | 2 (10.0) | 5 (25.0) | 4 (12.5)
Gastrointestinal Disorders | Nausea | 4 (12.9) | 11 (28.2) | 0 (0.0) | 0 (0.0) | 1 (3.1)
Gastrointestinal Disorders | Vomiting NOS | 1 (3.2) | 3 (7.7) | 0 (0.0) | 0 (0.0) | 0 (0.0)
General Disorders and Administration Site Conditions | Rigors | 7 (22.6) | 7 (17.9) | 0 (0.0) | 0 (0.0) | 0 (0.0)
-- | Feeling cold | 4 (12.9) | 6 (15.4) | 0 (0.0) | 0 (0.0) | 0 (0.0)
-- | Pain NOS | 1 (3.2) | 5 (12.8) | 0 (0.0) | 0 (0.0) | 0 (0.0)
-- | Feeling hot | 3 (9.7) | 1 (2.6) | 0 (0.0) | 0 (0.0) | 0 (0.0)
-- | Asthenia | 2 (6.5) | 2 (5.1) | 0 (0.0) | 0 (0.0) | 1 (3.1)
-- | Pyrexia | 2 (6.5) | 1 (2.6) | 0 (0.0) | 0 (0.0) | 0 (0.0)
-- | Fatigue | 0 (0.0) | 2 (5.1) | 0 (0.0) | 0 (0.0) | 1 (3.1)
-- | Edema peripheral | 0 (0.0) | 0 (0.0) | 0 (0.0) | 1 (5.0) | 0 (0.0)
Metabolism and Nutrition Disorders | Appetite decreased NOS | 2 (6.5) | 2 (5.1) | 0 (0.0) | 0 (0.0) | 0 (0.0)
Musculoskeletal and Connective Tissue Disorders | Muscle spasm | 2 (6.5) | 2 (5.1) | 0 (0.0) | 1 (5.0) | 0 (0.0)
-- | Back pain | 2 (6.5) | 2 (5.1) | 0 (0.0) | 0 (0.0) | 0 (0.0)
Nervous System Disorders | Headache | 17 (54.8) | 23 (59.0) | 1 (5.0) | 4 (20.0) | 3 (9.4)
-- | Dizziness | 5 (16.1) | 7 (17.9) | 1 (5.0) | 0 (0.0) | 1 (3.1)
-- | Paraesthesia | 2 (6.5) | 1 (2.6) | 0 (0.0) | 0 (0.0) | 0 (0.0)
-- | Tremor | 1 (3.2) | 2 (5.1) | 0 (0.0) | 0 (0.0) | 0 (0.0)
Skin and Subcutaneous Tissue Disorders | Sweating increased | 3 (9.7) | 2 (5.1) | 0 (0.0) | 0 (0.0) | 0 (0.0)
Vascular Disorders | Pallor | 1 (3.2) | 3 (7.7) | 0 (0.0) | 0 (0.0) | 0 (0.0)
*Adverse events that occurred during or within 3 days of VIGIV or placebo administration.
a 0.9% NaCl infused at 2 mL/min.
b Infusion rate: 4 mL/min; subjects were fasted.
c Infusion rate: 4 mL/min or 2 mL/min; subjects were fasted.
d Infusion rate: 2 mL/min; subjects were not fasted.

Most adverse reactions were of mild intensity (defined in study protocols as awareness of a sign or symptom but subject can tolerate). One subject in the 9000 Units per kg dosage group experienced syncope.

There was a lower incidence of adverse reactions when VIGIV (9000 Units per kg) was infused at 2 mL/min than 4 mL/min. There was a higher incidence of adverse reactions after administration of VIGIV in fasted subjects compared to subjects that were not fasted overnight.

There were no serious adverse reactions or adverse reactions of severe intensity in the clinical studies. There were no instances of VIGIV discontinuation due to an adverse event, or reduction in dose or infusion rate.

6.2 Post-marketing Experience

Because post-marketing adverse reactions are reported voluntarily from a population of uncertain size, it is not always possible to reliably estimate their frequency or establish a causal relationship to exposure to the product.

Severe vaccinia infection that developed possible intravascular hemolysis and transient renal injury has been reported. As VIGIV may contain blood group antigens that may have hemolysins, VIGIV doses may have contributed to the hemolysis. However, the hemolysis did not reoccur with continued VIGIV dosing. Mild and transient chest pain that occurred the same day of VIGIV infusion has been reported.

The following are adverse reactions listed by body system that have been identified and reported during the post-approval use of other IGIV products:

- Cardiovascular: Cardiac arrest, tachycardia
- Hematologic and Lymphatic: Neutropenia, leukopenia, anemia, lymphadenopathy
- Integumentary: Stevens-Johnson syndrome, epidermolysis, erythema multiforme, dermatitis (e.g., bullous dermatitis), urticaria or other skin reactions
- Gastrointestinal: Hepatic dysfunction, abdominal pain, diarrhea
- Muscular: Myalgia, arthralgia
- Neurological: Coma, loss of consciousness, seizures
- Renal: Acute kidney injury, osmotic nephropathy
- Respiratory: Apnea, Acute Respiratory Distress Syndrome (ARDS), cyanosis, hypoxemia, pulmonary edema, dyspnea, bronchospasm, wheezing
- General/Body as a Whole: Malaise, chest discomfort

7 DRUG INTERACTIONS

7.1 Live, Attenuated Vaccines

Immune globulin administration may impair the efficacy of live attenuated vaccines such as measles, rubella, mumps and varicella. Defer vaccination with live virus vaccines until approximately three months after administration of VIGIV. Revaccinate people who received VIGIV shortly after live virus vaccination three months after the administration of the VIGIV.

7.2 Drug/Laboratory Interactions

- VIGIV contains maltose, which can be misinterpreted as glucose by certain types of blood glucose testing systems (for example, those based on the GDH-PQQ or glucose-dye-oxidoreductase methods). Due to the potential for falsely elevated glucose readings, only use testing systems that are glucose-specific to test or monitor blood glucose levels in patients receiving VIGIV [see BOXED WARNING and 5.3 Blood Glucose Monitoring].
- Antibodies present in VIGIV may interfere with some serological tests. After administration of immune globulins like VIGIV, a transitory increase of passively transferred antibodies in the patient’s blood may result in positive results in serological testing (e.g. Coombs’ test) [see 5.5 Hemolysis].

8 USE IN SPECIFIC POPULATIONS

8.1 Pregnancy

Risk Summary

There are no data on the use of VIGIV in pregnant women to inform on drug-associated risk. Animal reproduction studies have not been conducted with VIGIV.

8.2 Lactation

Risk Summary

There are no data to assess the presence or absence of VIGIV in human milk, the effects on the breastfed child or the effects on milk production/excretion.

8.4 Pediatric Use

Safety and effectiveness in the pediatric population (<16 yrs of age) has not been established for VIGIV.

8.5 Geriatric Use

Safety and effectiveness in the geriatric population (>65 yrs of age) has not been established for VIGIV.

11 DESCRIPTION

VIGIV is a solvent/detergent-treated, filtered sterile solution of purified gamma globulin (IgG) fraction of human plasma containing antibodies to vaccinia virus. It is stabilized with 10% maltose and 0.03% polysorbate 80 (pH is between 5.0 and 6.5) and contains no preservative. The product is a clear to opalescent liquid.

VIGIV is manufactured from plasma collected from healthy, screened donors with high titers of anti-vaccinia antibody (meeting minimum potency specifications) that is purified by an anion-exchange column chromatography method (3, 4). The plasma donors were boosted with vaccinia vaccine prior to donating plasma used in the production of the product. Each plasma donation used for the manufacture of VIGIV is tested for the presence of hepatitis B virus (HBV) surface antigen (HBsAg) and antibodies to human immunodeficiency viruses (HIV) 1/2 and hepatitis C virus (HCV) using FDA-licensed serological tests.

Plasma used in the manufacture of this product was tested by FDA licensed Nucleic Acid Testing (NAT) for HIV-1 and HCV and found to be negative. A NAT for HBV was also performed on all Source Plasma used and found to be negative; however, the significance of a negative result has not been established. The Source Plasma has also been tested by NAT for hepatitis A virus (HAV) and parvovirus B19 and the limit for B19 in the manufacturing pool is set not to exceed 10^4 IU of B19 DNA per mL.

The manufacturing process contains two steps implemented specifically for virus clearance. The solvent and detergent step (using tri-n-butyl phosphate and Triton X-100) is effective in the inactivation of enveloped viruses, such as HBV, HCV and HIV (5). Virus filtration, using a Planova 20N virus filter, is effective for the removal of viruses based on their size, including some non-enveloped viruses (6). In addition to the two specific steps, the anion-exchange chromatography step contributes to the removal of small non–lipid enveloped viruses.

The inactivation and reduction of known enveloped and non–enveloped model viruses were validated in laboratory studies as summarized in Table 2.

Table 2 Virus Reduction Values (Log10) Obtained through Validation Studies
Virus | Enveloped RNA HIV-1 | Enveloped RNA BVDV | Enveloped DNA PRV | Enveloped DNA Vaccinia | Non-Enveloped RNA HAV | Non-Enveloped RNA EMC | Non-Enveloped DNA MMV | Non-Enveloped DNA PPV
Family | retro | flavi | herpes | pox | picorna | picorna | parvo | parvo
Size (nm) | 80–100 | 50–70 | 120–200 | 220–450 long x 140–260 wide | 25–30 | 30 | 20–25 | 18–24
Anion Exchange Chromatography; (partitioning) | Not evaluated | Not evaluated | Not evaluated | Not evaluated | 2.3 | n.e. | 3.4 | n.e.
20N Filtration; (size exclusion) | ≥4.7 | ≥3.5 | ≥5.6a | n.e. | n.e. | 4.8 | n.e. | 4.1
Solvent/Detergent; (inactivation) | ≥4.7 | ≥7.3 | ≥5.5 | ≥3.7 | Not evaluated | Not evaluated | Not evaluated | Not evaluated
Total Reduction (log10) | ≥9.4 | ≥10.8 | ≥11.1 | ≥3.7 | 7.1 | 7.1 | 7.5 | 7.5
BVDV: bovine viral diarrhea virus; model virus for hepatitis C virus (HCV) and West Nile virus (WNV); EMC: encephalomyocarditis virus; model for HAV and for small non-enveloped viruses in general; HAV: human hepatitis A virus; relevant virus for HAV and model for small non-enveloped viruses in general; HIV-1: human immunodeficiency virus-1; relevant virus for human immunodeficiency virus-1 and model for HIV-2; MMV: murine minute virus; model for human parvovirus B19 and for small non-enveloped viruses in general; n.e.: not evaluated; PPV: porcine parvovirus; model for human parvovirus B19 and for small non-enveloped viruses in general; PRV: pseudorabies virus; model for large enveloped DNA viruses, including herpes
a The PRV was retained by the 0.1 µm pre-filter during the virus validation. Since manufacturing employs a 0.1 µm pre-filter before the 20N filter, the claim of ≥5.6 reduction is considered applicable.

The product potency (as determined by a plaque reduction neutralization test) is expressed in arbitrary units (U) by comparison to the FDA reference standard. Each vial contains approximately 40 to 80 mg/mL total protein and ≥50,000 units of vaccinia antibody neutralizing activity. The product contains ≤40 mcg/mL of Immune globulin A (IgA).

12 CLINICAL PHARMACOLOGY

12.1 Mechanism of Action

VIGIV provides passive immunity for individuals with complications to vaccinia virus vaccination. The exact mechanism of action is not known.

12.2 Pharmacodynamics

Two double-blind pharmacodynamic studies were conducted in which 82 healthy volunteers were randomized to receive vaccinia vaccination with or without VIGIV.

In the first study, the efficacy of 9000 Units per kg of VIGIV on the immunologic and local response to Dryvax was evaluated. A total of 32 healthy subjects were randomized to receive single IV infusions of either VIGIV (9000 Units per kg) or Placebo (0.9% Sodium Chloride Injection USP) on Day 0, and either Placebo or VIGIV (9000 Units per kg) concurrently with vaccinia (Dryvax) vaccination on Day 4.

In a second study, 50 healthy subjects were randomized to receive a single IV infusion of either VIGIV (9000 Units per kg), VIGIV (24,000 Units per kg), or Placebo (0.9% Sodium Chloride Injection USP) on Day 0, and either placebo or vaccinia (Dryvax) vaccination on Day 4.

The effect of VIGIV on the immunologic response to Dryvax was determined by measuring vaccinia antibody titer (vaccinia IgG) in plasma and comparing titer levels across all three treatment arms. In addition, the effect of VIGIV on the local response (tissue) to Dryvax was assessed by evaluating the size of the pox reaction, as well as the area of erythema and induration following vaccination.

VIGIV (9000 Units per kg and 24,000 Units per kg) reduced the local and immunological response to vaccinia vaccination when it was administered 4 days prior to vaccination compared to vaccination alone. This is consistent with the hypothesis that VIGIV can neutralize vaccinia virus in vivo [see 14 CLINICAL STUDIES]. In addition, infusions of VIGIV of up to 24,000 Units per kg were well tolerated [see 6.1 Clinical Trials Experience].

12.3 Pharmacokinetics

A double-blind study was conducted in which 60 healthy subjects were randomized to receive either 6000 Units per kg or 9000 Units per kg VIGIV. After intravenous administration of 6000 Units per kg to 31 healthy subjects, a mean peak plasma concentration of 161 Units per mL was achieved within two hours. The half-life of VIGIV was 30 days (range of 13 to 67 days) and the volume of distribution was 6630 mL. Pharmacokinetic parameters were calculated based on antibody levels determined by an ELISA.

The levels of vaccinia immune globulin remained in circulation for a prolonged period of time, with a mean half-life ranging from approximately 26 to 30 days. Maximum plasma concentrations (Cmax) of VIGIV reached levels ranging from approximately 160 to 232 Units per mL in 1.8 to 2.6 hours. In addition, the drug had a large volume of distribution, as demonstrated by both non-compartmental and compartmental analyses.

Non-compartmental analyses demonstrated that at the two dose levels studied, the drug exhibited dose-proportionality (AUC and Cmax values) (Table 3). The pharmacokinetic parameters estimated by compartmental analysis were similar to those calculated by non-compartmental methods.

Table 3 Non-compartmental Pharmacokinetic Parameters (mean (±SD)) Using VIGIV (6000 U/kg or 9000 U/kg) from Measured Data Arithmetic Mean (±SD)
Parameter | 6000 U/kg | 9000 U/kg
AUC0 - ∞ (U*h/mL) | 58521 (16079) | 78401 (17502)
AUC0-t (U*h/mL) | 49405 (13246) | 71541 (13173)
CMAX (U/mL) | 161 (40.0) | 232 (40.9)
TMAX (h) | 1.84 (1.12) | 2.61 (2.41)
T½ (days) | 30.0 (10.0) | 26.2 (5.08)

The plasma concentration of circulating VIGIV was also compared to a theoretical value obtained from a model of previously licensed Baxter Vaccinia Immune Globulin (VIG) product at Day 5 after IV administration of VIGIV. Since Baxter VIG was administered intramuscularly (IM) and VIGIV is administered IV, the comparison was made at approximately five days to account for equilibration between the extravascular and intravascular compartments following IM injection.

The binding capacity and neutralizing antibody activity of anti-vaccinia antibody in these subjects five days after intravenous administration of VIGIV (both 6000 Units per kg and 9000 Units per kg dosages) were at least as high as the theoretical values that would be achieved following the intramuscular administration of the comparator VIG (see Table 4). Five days represents the approximate time of peak serum anti-vaccinia antibody concentration following intramuscular administration of other Immune Globulin (Human) products. No historical pharmacokinetic data are available for the theoretical intramuscular comparator VIG.

Table 4 Test of Non-inferiority
Dose VIGIV (U/kg) | Plasma Levels, U/mL (Rangea) VIGIVb | Plasma Levels, U/mL (Rangea) VIGIMc | Ratio of Means % (97.5% Lower Confidence Interval Bound)d
6000 | 60.1 (36.1–84.6) | 66.2 (42.3–94.9) | 90.82 (86.94)
9000 | 90.3 (63.4–133.8) | 64.8 (47.6–87.2) | 139.40 (135.27)
a Geometric mean (range)
b Observed levels
c Simulated levels
d Expressed as a percentage relative to the geometric mean of the simulated concentrations at Day 5 after 6000 U/kg intramuscular administration

13 NONCLINICAL TOXICOLOGY

13.1 Carcinogenesis, Mutagenesis, Impairment of Fertility

Carcinogenicity, genotoxicity and fertility studies have not been conducted with VIGIV.

13.2 Animal Toxicology and/or Pharmacology

The efficacy of VIGIV against vaccinia virus in a mouse-tail lesion model was assessed. A range of doses of VIGIV and a previously licensed VIG were compared for their ability to reduce pox formation in this model.

Using this model, it was demonstrated that VIGIV exerted an in vivo protective effect against vaccinia infection when compared to a negative control. In addition, when using the mouse-tail lesion model with two different strains of vaccinia virus, it was observed that the protective effect of VIGIV appeared similar to that of the previously licensed VIG and a CBER reference standard.

A single study in rabbits has demonstrated increased corneal scarring upon intramuscular vaccinia immune globulin administration in vaccinia keratitis (7).

Since VIGIV is a product of human origin, secondary pharmacodynamics, safety pharmacology and pharmacodynamic drug interactions were not investigated in animals.

14 CLINICAL STUDIES

The pharmacokinetic, pharmacodynamic and safety profiles of VIGIV were evaluated in three clinical trials. In these clinical studies, VIGIV was shown to have an acceptable safety profile when administered as single infusions of 6000 Units per kg, 9000 Units per kg or 24,000 Units per kg to healthy subjects. For the safety/pharmacokinetics study, see 12.3 Pharmacokinetics.

14.1 Pharmacodynamic Effect of VIGIV on Immune and Local Responses to Dryvax

In a randomized, single center, double-blind study with three parallel treatment arms, the efficacy of 9000 Units per kg of VIGIV on the immunologic and local response to the smallpox vaccine Dryvax was evaluated. Thirty-two healthy female and male subjects were randomized to receive single IV infusions of either VIGIV (9000 Units per kg) or Placebo (0.9% Sodium Chloride Injection USP) on Day 0, and either Placebo or VIGIV (9000 Units per kg) concurrently with vaccinia (Dryvax) vaccination on Day 4.

In this study, the curves for antibody titre vs. time were similar between administration of VIGIV four days prior to vaccination with Dryvax and concurrent administration of VIGIV with Dryvax.

Based on area under the effective time curve from Day 4 to 32 (AUEC4-32) results, the administration of VIGIV four days prior to vaccination with Dryvax slightly reduced the pox reaction and erythema area by 4 to 9% and 8 to 12%, respectively, as compared to the concurrent administration of VIGIV with the Dryvax vaccine, or with Dryvax alone.

In an additional randomized, single center, double-blind, study with five parallel treatment arms, the efficacy of two different doses of VIGIV (9000 Units per kg and 24,000 Units per kg) on the immunologic and local response to Dryvax was evaluated.

Fifty healthy subjects were randomized to receive a single IV infusion of either VIGIV (9000 Units per kg), VIGIV (24,000 Units per kg), or Placebo (0.9% Sodium Chloride Injection USP) on Day 0, and either placebo or vaccinia (Dryvax) vaccination on Day 4.

The administration of VIGIV four days prior to vaccinia vaccination decreased the endogenous immune response to Dryvax in a dose-dependent manner. In addition, the mean pox reaction and erythema area diameters were smaller in size when 24,000 Units per kg of VIGIV was administered prior to vaccination with Dryvax compared to those when 9000 Units per kg of VIGIV was administered prior to vaccination with Dryvax or to those from administration of Dryvax alone. These data are consistent with the hypothesis of vaccinia virus neutralization in vivo by VIGIV.

15 REFERENCES

1. Kahwaji J et al., Acute Hemolysis after High-Dose Intravenous Immunoglobulin Therapy in Highly HLA Sensitized Patients. Clin J Am Soc Nephrol. 2009 December 4;1993–97.
2. Daw Z, Padmore R, Neurath D, et al. Hemolytic transfusion reactions after administration of intravenous immune (gamma) globulin: A case series analysis. Transfusion 2008;48:1598-601.
3. Bowman JM, Friesen AD, Pollock JM, Taylor WE. WinRho: Rh immune globulin prepared by ion exchange for intravenous use. Canadian Med Assoc J. 1980;123:1121-5.
4. Friesen AD, Bowman JM, Price HW. Column ion-exchange preparation and characterization of an Rh immune globulin (WinRho) for intravenous use. Journal Appl Biochem. 1981;3:164-75.
5. Horowitz B. Investigations into the application of tri(n-butyl)phosphate/detergent mixtures to blood derivatives. Curr Stud Hematol Blood Transfus. 1989;56:83-96.
6. Burnouf T. Value of virus filtration as method for improving the safety of plasma products. Vox Sang. 1996;70:235-6.
7. Fulginiti VA, Winograd LA, Jackson M, Ellis P. Therapy of experimental vaccinal keratitis: Effect of idoxuridine and VIG. Arch Ophthal. 1965;74:539-44.

16 HOW SUPPLIED/STORAGE AND HANDLING

16.1 How Supplied

NDC 60492-0173-1: 20 mL glass vial

NDC 60492-0173-2: Shelf carton containing 24 glass vials

The product is supplied as a 20 mL single dose vial containing ≥50,000 Units per vial. It is packaged in a shelf carton with 24 vials and four package inserts.

VIGIV does not contain natural rubber latex.

16.2 Storage and Handling

Product is stored frozen at or below -15°C (≤5°F). Do not use after expiration date. Use within 60 days of thawing at 2°C to 8°C (36°F to 46°F). Begin intravenous infusion within 4 hours after entering the vial.

Do not reuse or save VIGIV for future use. This product contains no preservative; therefore, discard partially used vials.

17 PATIENT COUNSELING INFORMATION

Discuss the risks and benefits of VIGIV with the patient before prescribing or administration.

- Inform patients of the potential for hypersensitivity reactions, especially in individuals with previous reactions to human immune globulin and in individuals deficient in IgA [see 4 CONTRAINDICATIONS and 5.1 Hypersensitivity]. Advise patients to be aware of the following symptoms associated with allergic reactions: hives, rash, chest tightness, wheezing, shortness of breath, or feeling light headed or dizzy when they stand. Caution patients to seek medical attention immediately should they experience any one or more of the above mentioned symptoms, as well as other side effects including injection site pain, chills, fever, headache, nausea, vomiting, and joint pain.
- Advise patients that the maltose contained in VIGIV can interfere with some types of blood glucose monitoring systems. Patients must use testing systems that are glucose-specific for monitoring blood glucose levels as the interference of maltose could result in falsely elevated glucose readings, which could lead to untreated hypoglycemia or to inappropriate insulin administration, resulting in life-threatening hypoglycemia [see 5.3 Blood Glucose Monitoring].
- Advise patients that VIGIV may impair the effectiveness of certain live virus vaccines such as measles, rubella (i.e. German measles), mumps, and varicella (i.e. chickenpox). Patients recently vaccinated must notify their treating physician [see 7.1 Live, Attenuated Vaccines].
- Inform patients that VIGIV is prepared from human plasma. Products made from human plasma may contain infectious agents such as viruses that can cause disease. The risk that such products will transmit an infectious agent has been reduced by screening plasma donors for prior exposure to certain viruses, by testing for the presence of certain current virus infections, and by inactivating and/or removing certain viruses during manufacturing. Despite these measures, such products can still potentially transmit disease. There is also the possibility that unknown infectious agents may be present in such products [see 5.8 Transmissible Infectious Agents].

Manufactured by:

Emergent BioSolutions Canada Inc.
155 Innovation Drive
Winnipeg, Manitoba
Canada, R3T 5Y3

U.S. License No. 2084